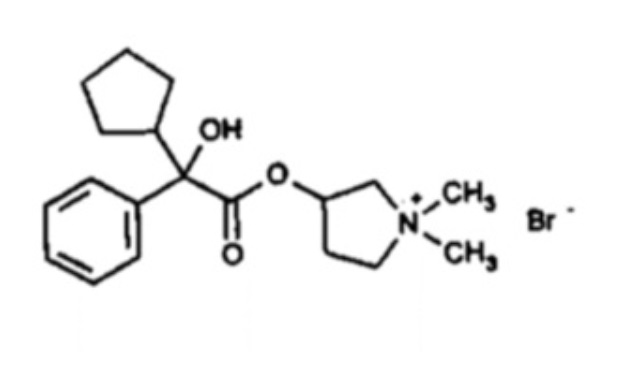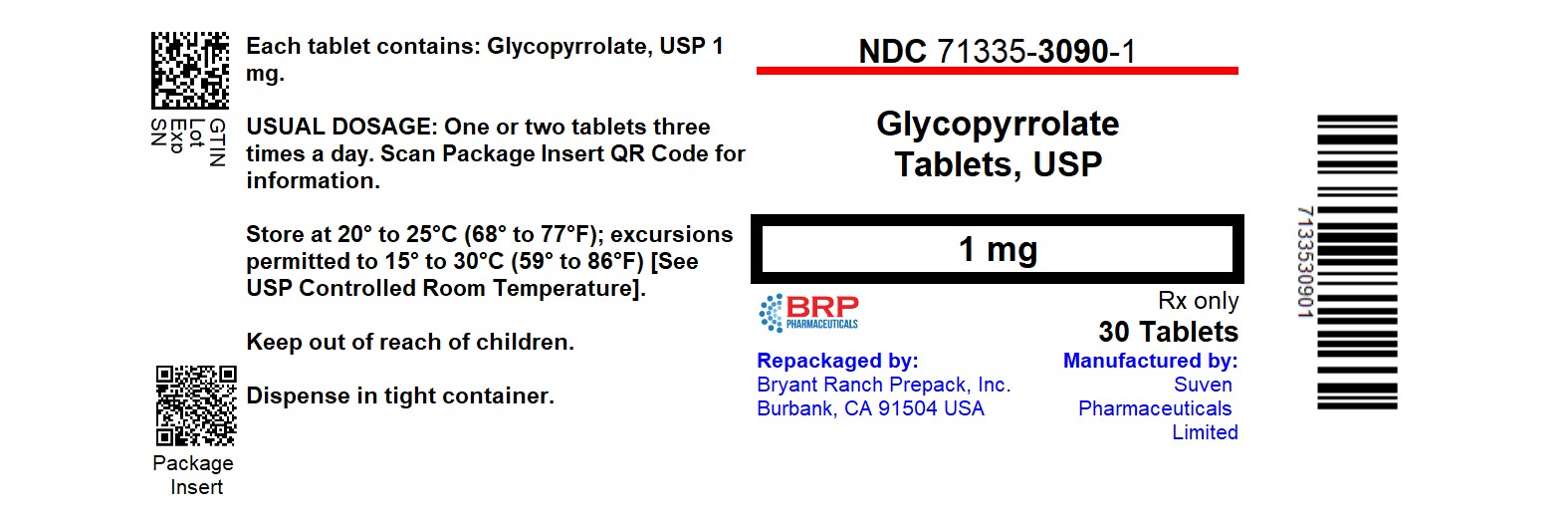 DRUG LABEL: Glycopyrrolate
NDC: 71335-3090 | Form: TABLET
Manufacturer: Bryant Ranch Prepack
Category: prescription | Type: HUMAN PRESCRIPTION DRUG LABEL
Date: 20260217

ACTIVE INGREDIENTS: GLYCOPYRROLATE 1 mg/1 1
INACTIVE INGREDIENTS: ANHYDROUS DIBASIC CALCIUM PHOSPHATE; LACTOSE MONOHYDRATE; MAGNESIUM STEARATE; POVIDONE, UNSPECIFIED; SODIUM STARCH GLYCOLATE TYPE A POTATO

HIGHLIGHTS OF PRESCRIBING INFORMATION

These highlights do not include all the information needed to use GLYCOPYRROLATE safely and effectively. See full prescribing information for GLYCOPYRROLATE.
GLYCOPYRROLATE tablets, for oral use
Initial U.S. Approval: 1961

1 INDICATIONS & USAGE

Glycopyrrolate are anticholinergics indicated in adults to reduce symptoms of a peptic ulcer as an adjunct to treatment of peptic ulcer. (1)
Limitations of Use:
Not indicated as monotherapy for the treatment of peptic ulcer because effectiveness in peptic ulcer healing has not been established. (1)

2 DOSAGE & ADMINISTRATION

Important Dosing Information (2.1)
• Glycopyrrolate is not recommended for patients initiating treatment or receiving maintenance treatment with glycopyrrolate or another 1 mg dosage strength of oral glycopyrrolate tablets.
Recommended Dosage (2.2)
• The recommended initial dosage of glycopyrrolate is 1 mg three times daily (in the morning, early afternoon, and at bedtime). Some patients may require 2 mg at bedtime to assure overnight control of symptoms. For maintenance, a dosage of 1 mg twice a day is frequently adequate.
• The recommended dosage of glycopyrrolate for adults is 2 mg two or three times daily at equally spaced intervals.
• The maximum recommended daily dosage is 8 mg.
• Use the lowest effective dosage of glycopyrrolate to control symptoms. If patients can be titrated to a lower dose, switch from glycopyrrolate or another 1 mg oral tablet of glycopyrrolate.

3 DOSAGE FORMS & STRENGTHS

• Tablets: 1 mg (functionally scored) and 2 mg (3)

4 CONTRAINDICATIONS

• Patients at risk for anticholinergic toxicity due to various underlying medical conditions. (4, 5.1, 5.2, 5.3)
• Hypersensitivity to glycopyrrolate or the inactive ingredients. (4)

5 WARNINGS AND PRECAUTIONS

• Precipitation of Acute Glaucoma: May increase intraocular pressure; if symptoms occur, discontinue use and promptly seek medical care. (4, 5.1)
• Partial or Complete Mechanical Intestinal Obstruction: Diarrhea may be an early symptom, especially in patients with ileostomy or colostomy. If the obstruction is suspected, discontinue use and evaluate the patient for obstruction. (4, 5.2)
• GI Adverse Reactions Due to Decreased GI Motility: Delayed gastric emptying, constipation, and intestinal pseudo-obstruction may occur and precipitate or aggravate paralytic ileus and toxic megacolon; not recommended for use with anticholinergics or other medications that decrease GI peristalsis. (4, 5.3, 7.1)
• Cognitive and Visual Adverse Reactions: May impair mental and/or physical function. Inform patients not to operate motor vehicles or perform other hazardous tasks until reasonably certain they are not adversely affected; discontinue use if signs or symptoms develop. (5.4, 7.1)
• Heat Prostration at High Environmental Temperatures: Heat prostration resulting in fever and heatstroke can occur, especially in geriatric patients. Avoid exposure to hot or very warm environmental temperatures. (5.5, 5.7)
• Other Conditions Exacerbated by Anticholinergic Adverse Reactions: Use is not recommended in patients with autonomic neuropathy, hyperthyroidism, cardiac disease, hiatal hernia, etc. (5.6, 7.1)
• Increased Risk of Anticholinergic Adverse Reactions in Geriatric Patients: Complications include urinary retention, bowel obstruction, heat prostration, arrhythmias, delirium, and falls or fractures. Not recommended in geriatric patients and may be contraindicated in some patients with underlying medical conditions. (4, 5.7, 8.5)

6 ADVERSE REACTIONS

Adverse reactions include blurred vision, drowsiness, decreased sweating, flushing, vomiting, constipation, dry mouth, tachycardia, and urinary retention. (6)
To report SUSPECTED ADVERSE REACTIONS, contact Rising Pharma Holdings, Inc. at 1-844-874-7464 or FDA at 1-800-FDA-1088 or www.fda.gov/medwatch.

7 DRUG INTERACTIONS

• Other Anticholinergic Drugs: Concomitant use is not recommended. (5.3, 5.4, 5.6, 7.1)
• Drugs with Altered Absorption due to Decreased GI Motility: Concomitant use is not recommended. (7.2)
• GI Toxicity with Solid Oral Dosage Forms of Potassium Chloride: Concomitant use is not recommended. (7.3)

8 USE IN SPECIFIC POPULATIONS

• Renal Impairment: Monitor patients with renal impairment; if anticholinergic adverse reactions occur, discontinue use. (8.6)

FULL PRESCRIBING INFORMATION

1 INDICATIONS & USAGE

Glycopyrrolate are indicated in adults to reduce symptoms of a peptic ulcer as an adjunct to treatment of peptic ulcer.
Limitations of Use
Glycopyrrolate are not indicated as monotherapy for the treatment of peptic ulcer because effectiveness in peptic ulcer healing has not been established.

2 DOSAGE & ADMINISTRATION

2.1 Important Dosing Information

• Glycopyrrolate is not recommended for patients in whom a lower dosage strength of oral glycopyrrolate (e.g., glycopyrrolate or another 1 mg tablet strength) is appropriate for initial or maintenance treatment because the dosage strength of glycopyrrolate may exceed the recommended initial and maintenance dosage of oral glycopyrrolate tablets.

2.2 Recommended Dosage

• The recommended initial dosage of glycopyrrolate for adults is 1 mg three times daily (in the morning, early afternoon, and at bedtime). Some patients may require 2 mg at bedtime to assure overnight control of symptoms. For maintenance, a dosage of 1 mg twice a day is frequently adequate.
• The recommended dosage of glycopyrrolate for adults is 2 mg two or three times daily at equally spaced intervals.
• The maximum recommended daily dosage of glycopyrrolate is 8 mg.
• Use the lowest effective dosage of glycopyrrolate to control symptoms. If patients can be titrated to a lower dose, switch from glycopyrrolate or another 1 mg oral tablet of glycopyrrolate.

3 DOSAGE FORMS & STRENGTHS

Tablets:
• 1 mg, white, round, flat-faced, beveled-edge tablet, debossed “CS” and “007” on one side and functionally scored on the other side.
• 2 mg, white, round, flat-faced, beveled-edge tablet, debossed “CS” score “008” on one side and plain on the other side.

4 CONTRAINDICATIONS

Glycopyrrolate are contraindicated in:
• Patients at risk for anticholinergic toxicity due to an underlying medical condition, including:
o Glaucoma [see Warnings and Precautions (5.1)]
o Obstructive uropathies, including prostatic hypertrophy
o Mechanical obstructive diseases of the gastrointestinal tract (e.g., pyloroduodenal stenosis, strictures) [see Warnings and Precautions (5.2)]
o Gastrointestinal motility disorders (e.g., achalasia, paralytic ileus, intestinal atony) [see Warnings and Precautions (5.3)]
o Bleeding gastrointestinal ulcer
o Active inflammatory or infectious colitis which can lead to toxic megacolon
o History of or current toxic megacolon
o Myasthenia gravis
• Patients with a hypersensitivity to glycopyrrolate or any of the inactive ingredients in glycopyrrolate [see Adverse Reactions (6) and Description (11)].

5 WARNINGS AND PRECAUTIONS

5.1 Precipitation of Acute Glaucoma

Glycopyrrolate may cause increased intraocular pressure in patients with glaucoma and reduce the effects of antiglaucoma agents. Instruct patients to discontinue glycopyrrolate and promptly seek medical care if they experience symptoms of acute angle-closure glaucoma (pain and reddening of the eyes accompanied by dilated pupils) [see Contraindications (4)].

5.2 Partial or Complete Mechanical Intestinal Obstruction

Glycopyrrolate may worsen intestinal mechanical obstruction, and diarrhea may be an early symptom of incomplete intestinal obstruction, especially in patients with ileostomy or colostomy. If partial or complete intestinal obstruction is suspected, discontinue the use of glycopyrrolate and evaluate for potential intestinal obstruction [see Contraindications (4)].

5.3 Gastrointestinal Adverse Reactions Due to Decreased Gastrointestinal Motility

Glycopyrrolate reduces gastrointestinal motility and may result in delayed gastric emptying, constipation, and intestinal pseudo-obstruction and may precipitate or aggravate paralytic ileus and toxic megacolon [see Contraindications (4)]. The risk of gastrointestinal adverse reactions is further increased with the use of other anticholinergics and other medications that decrease gastrointestinal peristalsis.
Monitor patients for symptoms of decreased gastrointestinal motility. Concomitant use of glycopyrrolate and other anticholinergics or other medications that decrease GI peristalsis is not recommended [see Drug Interactions (7.2)].

5.4 Cognitive and Visual Adverse Reactions

Glycopyrrolate may produce drowsiness and blurred vision and impair the mental and/or physical abilities required for the performance of hazardous tasks such as driving a motor vehicle, operating machinery, or performing other hazardous work [see Adverse Reactions (6)]. Concomitant use of other drugs that have anticholinergic properties may increase these effects [see Drug Interactions (7.1)].
Inform patients not to operate motor vehicles or other dangerous machinery or perform other hazardous tasks until they are reasonably certain that glycopyrrolate does not affect them adversely.
Discontinue glycopyrrolate if signs or symptoms of cognitive or visual impairment develop.

5.5 Heat Prostration at High Environmental Temperatures

In the presence of a high environmental temperature, heat prostration resulting in fever and heatstroke can occur with the use of glycopyrrolate due to decreased sweating, particularly in geriatric patients [see Adverse Reactions (6)]. Advise patients to avoid exposure to hot or very warm environmental temperatures when taking glycopyrrolate. Glycopyrrolate are not recommended in geriatric patients [see Warnings and Precautions (5.7)].

5.6 Other Conditions Exacerbated by Anticholinergic Adverse Reactions

Glycopyrrolate are not recommended in patients with other conditions exacerbated by anticholinergic adverse reactions (e.g., autonomic neuropathy, hyperthyroidism, cardiac disease, and hiatal hernia associated with reflux esophagitis) and in patients taking other anticholinergic medications [see Drug Interactions (7.1)].

5.7 Increased Risk of Anticholinergic Adverse Reactions in Geriatric Patients

Geriatric patients 65 years of age and older are at increased risk of anticholinergic adverse reactions that may lead to complications of urinary retention, bowel obstruction, heat prostration, arrhythmias, delirium, and falls or fractures. Glycopyrrolate are not recommended in geriatric patients and may be contraindicated in some geriatric patients with underlying medical conditions [see Contraindications (4), Warnings and Precautions (5.2, 5.5), Adverse Reactions (6) and Use in Specific Populations (8.5)].

6 ADVERSE REACTIONS

The following serious or otherwise important adverse reactions are discussed elsewhere in the labeling:
• Precipitation of Acute Glaucoma [see Warnings and Precautions (5.1)]
• Partial or Complete Mechanical Intestinal Obstruction [see Warnings and Precautions (5.2)]
• Gastrointestinal Adverse Reactions due to Decreased Gastrointestinal Motility [see Warnings and Precautions (5.3)]
• Cognitive and Visual Adverse Reactions [see Warnings and Precautions (5.4)]
• Heat Prostration at High Environmental Temperatures [see Warnings and Precautions (5.5)]
• Other Conditions Exacerbated by Anticholinergic Adverse Reactions [see Warnings and Precautions (5.6)]
• Increased Risk of Anticholinergic Adverse Reactions in Geriatric Patients [see Warnings and Precautions (5.7)]
The following adverse reactions associated with the use of glycopyrrolate, or other anticholinergic drugs, were identified in clinical studies or postmarketing reports. Because some of these reactions are reported voluntarily from a population of uncertain size, it is not always possible to reliably estimate their frequency or establish a causal relationship to drug exposure.
Cardiac Disorders: chest, pain, hypertension, tachycardia
Endocrine Disorders: decreased sweating
Eye Disorders: blurred vision, cycloplegia, dilatation of the pupil, increased ocular tension
Gastrointestinal Disorders: bloated feeling, constipation, dry mouth, dysgeusia, nausea, vomiting
Immune System Disorders: anaphylaxis [see Contraindications (4)]
Nervous System Disorders: agitation, dizziness, drowsiness, headache, insomnia, mental confusion, nervousness, weakness
Respiratory Disorders: respiratory depression, throat irritation
Renal and Urinary Disorders: urinary hesitancy, urinary retention
Reproductive System and Breast Disorders: impotence, suppression of lactation
Vascular Disorders: flushing

7 DRUG INTERACTIONS

7.1 Other Anticholinergic Drugs

There is potential for an additive interaction between glycopyrrolate and concomitantly used anticholinergic drugs (e.g., tricyclic antidepressants, anti-epileptics, class I antiarrhythmics, anti-spasmodics, amantadine) resulting in increased anticholinergic adverse reactions. Co-administration of antipsychotics with glycopyrrolate may lead to worsening of tardive dyskinesia. Glycopyrrolate are not recommended in patients taking other anticholinergic drugs [see Warnings and Precautions (5.3, 5.4, 5.6)].

7.2 Drugs with Altered Absorption due to Decreased Gastrointestinal Motility and Increased Transit Time

Decreased gastrointestinal motility by glycopyrrolate may impact absorption of other drugs leading to increased or decreased drug exposure. Glycopyrrolate are not recommended in patients taking other drugs that are affected by altered gastrointestinal motility [see Warnings and Precautions (5.3)].

7.3 Gastrointestinal Toxicity with Solid Oral Dosage Forms of Potassium Chloride

Oral glycopyrrolate may worsen gastrointestinal mucosal injury reported with solid oral dosage forms of potassium chloride due to decreased gastric motility and increased transit time, leading to prolonged contact with the gastrointestinal mucosa. Glycopyrrolate are not recommended in patients taking solid oral dosage forms of potassium chloride.

8 USE IN SPECIFIC POPULATIONS

8.1 Pregnancy

Risk Summary
Over decades of use, there is an absence of published data on orally administered glycopyrrolate in pregnant women, including an absence of any reports of a drug-associated risk of major birth defects, miscarriage, or other adverse maternal or fetal outcomes. In animal studies, at non-maternally toxic doses of oral glycopyrrolate, there were no adverse developmental effects in rats or rabbits. A pre- and post-natal development study of oral glycopyrrolate in rats showed a decrease in pup mean bodyweight that recovered post nursing, with no other developmental effects observed (see Data).
The estimated background risk of major birth defects and miscarriage for the indicated population is unknown. All pregnancies have a background risk of birth defect, loss, or other adverse outcomes. In the U.S. general population, the estimated background risk of major birth defects and miscarriage in clinically recognized pregnancies is 2% to 4% and 15% to 20%, respectively.
Data
Animal Data
At non-maternally toxic doses of oral glycopyrrolate, there were no effects on embryo-fetal development or toxicity in rats or rabbits. A pre- and post-natal development study of oral glycopyrrolate in rats showed a decrease in pup mean bodyweight that recovered post nursing, with no other developmental effects observed.
In a published reproductive and developmental study, male and female rats were administered glycopyrrolate in the diet at 0 mg/kg/day, 32.5 mg/kg/day, 63 mg/kg/day, and 130 mg/kg/day for 3 weeks to 5 weeks and through up to three consecutive litters. There was no indication of abnormalities in the pups of treated dams. There was a decreased rate of conception and in survival rate at weaning for all treated animals in a dose-related manner. Diminished rates of conception may be due to diminished seminal secretion [see Nonclinical Toxicology (13.1)].

8.2 Lactation

Risk Summary
There are no data on the presence of glycopyrrolate in either human or animal milk, the effects on the breastfed infant, or the effects on milk production. As with other anticholinergic drugs, glycopyrrolate may cause suppression of lactation. The developmental and health benefits of breastfeeding should be considered along with the mother's clinical need for glycopyrrolate and any potential adverse effects on the breastfed infant from glycopyrrolate.

8.4 Pediatric Use

Safety and effectiveness in pediatric patients have not been established.

8.5 Geriatric Use

Geriatric patients 65 years of age and older may be more sensitive to the anticholinergic adverse reactions of glycopyrrolate leading to complications of urinary retention, bowel obstruction, heat prostration, arrhythmias, delirium, and falls or fractures; therefore, glycopyrrolate are not recommended in geriatric patients and may be contraindicated in some geriatric patients with underlying medical conditions [see Contraindications (4) and Warnings and Precautions (5)].

8.6 Renal Impairment

Glycopyrrolate is substantially excreted by the kidney [see Clinical Pharmacology (12.3)]. Monitor patients with renal impairment for anticholinergic adverse reactions [see Adverse Reactions (6)]. If anticholinergic adverse reactions occur, discontinue glycopyrrolate.

10 OVERDOSAGE

Signs and symptoms of glycopyrrolate overdosage are related to excessive anti-muscarinic anticholinergic activity and are generally peripheral (e.g., flushing, hyperthermia, tachycardia, ileus, urinary retention, loss of ocular accommodation, and light sensitivity due to mydriasis), but central nervous system toxicity (agitation, seizures, hyperthermia) may also occur.
If over-exposure occurs, call the Poison Control Center at 1-800-222-1222 for current information on the management of glycopyrrolate poisoning and overdosage.
Management of glycopyrrolate overdosage is based upon presenting signs and symptoms, including close observation for severe or life-threatening complications which may require respiratory and cardiovascular monitoring and support. Consider administration of activated charcoal and/or use of a reversible anticholinesterase as appropriate or recommended by Poison Control.

11 DESCRIPTION

Glycopyrrolate Tablets, USP contain synthetic anticholinergic glycopyrrolate. Glycopyrrolate is a quaternary ammonium compound with the following chemical name: 3-[(cyclopentyl hydroxyphenylacetyl)oxy]-1,1-dimethylpyrrolidinium bromide. The molecular formula for glycopyrrolate is C19H28BrNO3, the molecular weight is 398.3 g/mol, and the structural formula is:

Each glycopyrrolate tablet contains glycopyrrolate, USP 1 mg, as the active ingredient. Each glycopyrrolate tablet contains glycopyrrolate, USP 2 mg, as the active ingredient. The inactive ingredients are dibasic calcium phosphate, lactose monohydrate, magnesium stearate, povidone, and sodium starch glycolate.

12 CLINICAL PHARMACOLOGY

12.1 Mechanism of Action

Glycopyrrolate, an anticholinergic (antimuscarinic) agent, inhibits the action of acetylcholine on parietal cells in the stomach and decreases the volume and acidity of gastric secretions.

12.2 Pharmacodynamics

No formal pharmacodynamic studies have been conducted with glycopyrrolate.

12.3 Pharmacokinetics

Patients with Renal Impairment
In the published literature, glycopyrrolate 4 mcg/kg was administered intravenously (glycopyrrolate are not recommended for intravenous use) in uremic patients undergoing renal transplantation surgery. The mean AUC (10.6 mcg·h/L) and 24-hour urinary excretion (7%) for glycopyrrolate were significantly different from normal healthy adult subjects undergoing general surgery (3.7 mcg·h/L, and 65%, respectively) [see Use in Specific Populations (8.6)].

13 NONCLINICAL TOXICOLOGY

13.1 Carcinogenesis & Mutagenesis & Impairment Of Fertility

Reproduction studies in rats resulted in diminished rates of conception in a dose-related manner. Studies in dogs suggest that diminished rates of conception may be due to diminished seminal secretion, which is evident at high doses of glycopyrrolate.

16 HOW SUPPLIED/STORAGE AND HANDLING

Glycopyrrolate Tablets USP, 1 mg are white, round, flat-faced, beveled-edge tablet, debossed “CS” and “007” on one side and functionally scored on the other side. Available as

- NDC 71335-3090-1: 30 TABLETs in a BOTTLE
- NDC 71335-3090-2: 270 TABLETs in a BOTTLE
- NDC 71335-3090-3: 28 TABLETs in a BOTTLE
- NDC 71335-3090-4: 90 TABLETs in a BOTTLE
- NDC 71335-3090-5: 100 TABLETs in a BOTTLE

Store at controlled room temperature, 20°C to 25°C (68°F to 77°F); excursions permitted to 15°C to 30°C (59°F to 86°F) [see USP Controlled Room Temperature]. Keep out of reach of children.

Dispense in tight container.

Repackaged/Relabeled by:
Bryant Ranch Prepack
Burbank, CA 91504

17 PATIENT COUNSELING INFORMATION

Precipitation of Acute Glaucoma
Advise patients to discontinue glycopyrrolate and promptly seek medical care if they experience symptoms of acute angle-closure glaucoma (pain and reddening of the eyes accompanied by dilated pupils) [see Warnings and Precautions (5.1)].
Partial or Complete Mechanical Intestinal Obstruction
Advise patients to contact their healthcare provider if diarrhea occurs, especially in patients with ileostomy or colostomy [see Warnings and Precautions (5.2)].
Gastrointestinal Adverse Reactions Due to Decreased Gastrointestinal Motility
Inform patients that glycopyrrolate may cause adverse reactions related to decreased gastrointestinal motility and report to their healthcare provider if they experience symptoms such as vomiting, early satiety, abdominal distention, and constipation [see Warnings and Precautions (5.3)].
Cognitive and Visual Adverse Reactions
Inform patients that glycopyrrolate may cause cognitive or visual impairment and not operate motor vehicles or other dangerous machinery or perform other hazardous tasks until they are reasonably certain that glycopyrrolate do not affect them adversely. Advise patients to discontinue glycopyrrolate immediately and contact their healthcare provider if symptoms develop (e.g., drowsiness or blurred vision) [see Warnings and Precautions (5.4)].
Heat Prostration at High Environmental Temperatures
Inform patients that glycopyrrolate can reduce sweating, leading to the possibility of heat exhaustion or heat stroke. Advise patients to avoid exposure to hot or very warm environmental temperatures [see Warnings and Precautions (5.5)].
Distributed by:Rising Pharma Holdings, Inc.
East Brunswick, NJ 08816

Made in India

Neutral code: 4323147/TS/DRUGS/2025

Revised: 08/2025

PIA74409-04

PACKAGE LABEL

Glycopyrrolate 1mg Tablets